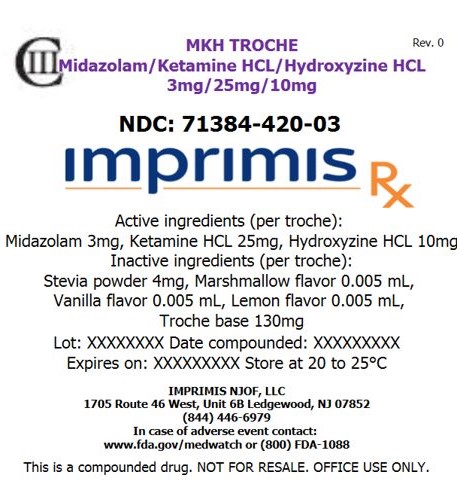 DRUG LABEL: MKH Dose Pack
NDC: 71384-420 | Form: TROCHE
Manufacturer: Imprimis NJOF, LLC
Category: prescription | Type: HUMAN PRESCRIPTION DRUG LABEL
Date: 20190305
DEA Schedule: CIII

ACTIVE INGREDIENTS: KETAMINE HYDROCHLORIDE 25 mg/1 1; MIDAZOLAM 3 mg/1 1; HYDROXYZINE HYDROCHLORIDE 10 mg/1 1

STORAGE AND HANDLING

Store at 20° to 25° C (68° to 77° F)